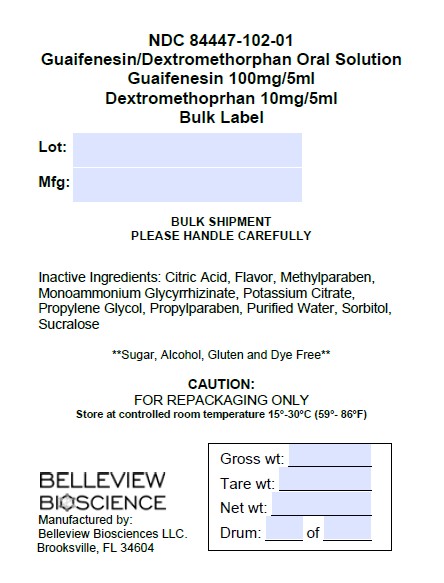 DRUG LABEL: Guaifenesin and Dextromethorphan HBr
NDC: 84447-102 | Form: LIQUID
Manufacturer: Belleview Biosciences
Category: otc | Type: HUMAN OTC DRUG LABEL
Date: 20240720

ACTIVE INGREDIENTS: GUAIFENESIN 100 mg/5 mL; DEXTROMETHORPHAN HYDROBROMIDE 10 mg/5 mL
INACTIVE INGREDIENTS: ANHYDROUS CITRIC ACID; AMMONIUM GLYCYRRHIZATE; PROPYLPARABEN; POTASSIUM CITRATE; METHYLPARABEN; WATER; SUCRALOSE; SORBITOL; PROPYLENE GLYCOL

Dextromethorphen and Guaifenesin

Directions:
■ follow dosage below or use as directed by a physician
■ do not take more than 6 doses in any 24-hour period

WARNINGS

Warnings: Do not use if you are now taking a prescription monoamine oxidase inhibitor (MADI)
(certain drugs for depression, psychiatric or emotional conditions, or Parkinson's disease),or for 2
weeks after stopping the MADI drug.If you do not know if your
prescription drug contains an MAOI; ask a doctor or pharmacist before taking this product.t
Ask a doctor before use if you have
■ cough that occurs with too much phlegm (mucus)
■ cough that lasts or is chronic, such as occurs with smoking, asthma,
chronic bronchitis, or emphysema
Stop use and ask doctor if

■cough lasts more than 7 days., comes back, or is accompanied by fever, rash, or persistent headache. These could be signs of a serious condition.
■you are hypersensitive to any of the ingredients.

If pregnant or breastfeeding, ask a health professional before use. Keep out of reach of children.
In case of overdose, get medical help or contact a Poison Control Center right away.

INACTIVE INGREDIENT

Inactive Ingredients: Citric Acid, Flavor, Methylparaben, Monoammonium Glycyrrhizinate, Potassium Citrate, Propylene Glycol, Propylparaben, Purified Water, Sorbitol, Sucralose

Uses:

■ helps loosen phlegm(mucus) and thin bronchial secretions to make coughs more productive

■ temporarily relieves cough due to minor throat and bronchial irritation as may occur with a cold

Keep out of reach of children. In case of overdose, get

medical help or contact a Poison Control Center right away.

Purpose:

Cough Suppressant and Expectorant

Active Ingredient (in each 5 mL tsp)

Dextromethorphan HBr 10mg

Guaifenesin 100mg

PACKAGE LABEL

NDC 84447-102-01

Guaifenesin/Dextromethorphan Oral Solution

Guaifenesin 100mg/5ml

Dextromethoprhan 10mg/5ml

PLEASE HANDLE CAREFULLY

Inactive Ingredients: Citric Acid, Flavor, Methylparaben, Monoammonium Glycyrrhizinate, Potassium Citrate, Propylene Glycol, Propylparaben, Purified Water, Sorbitol, Sucralose

**Sugar, Alcohol, Gluten and Dye Free**

CAUTION:

FOR REPACKAGING ONLY

Store at controlled room temperature 15°-30°C (59°- 86°F)